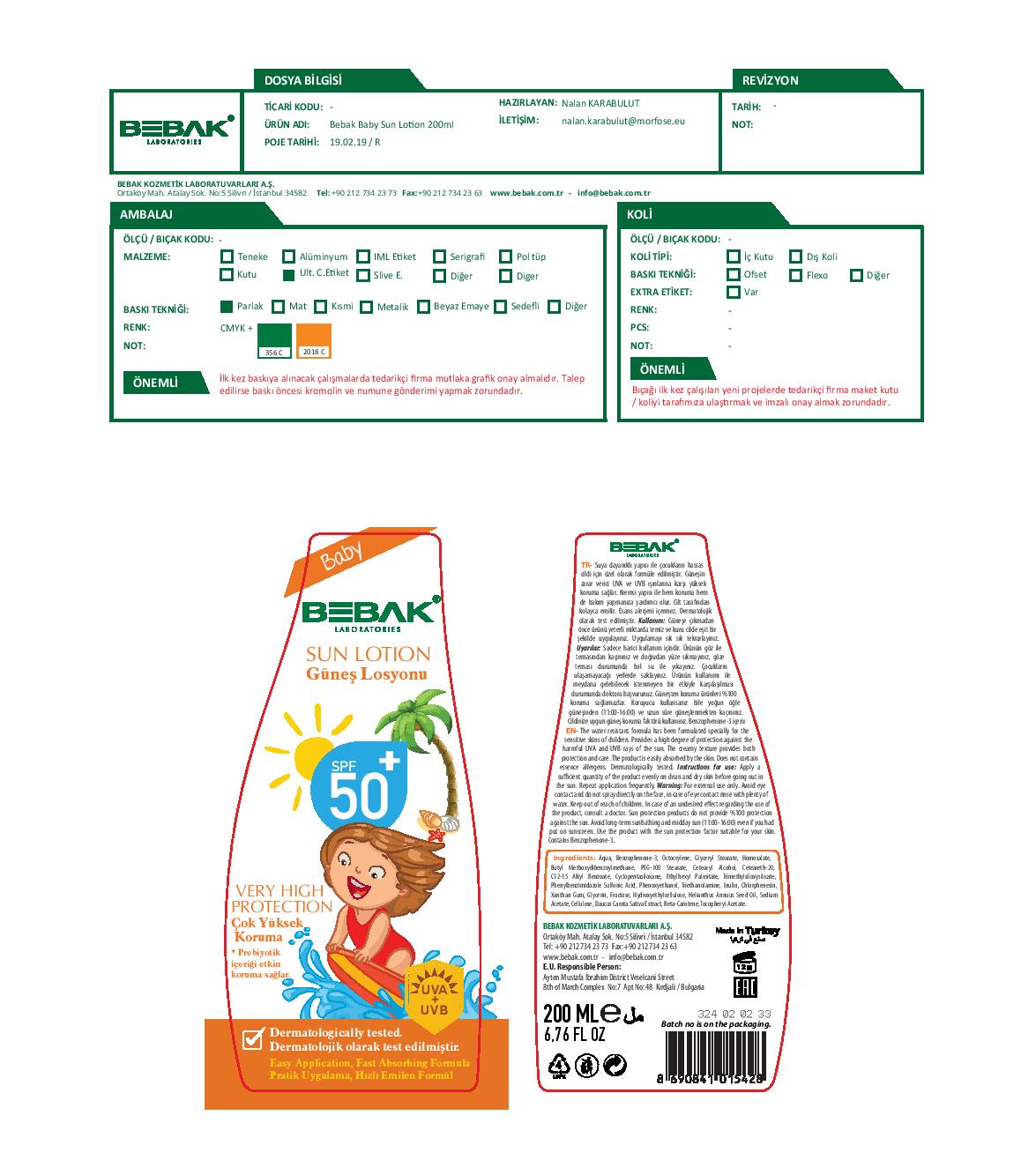 DRUG LABEL: Bebak Baby Sun
NDC: 77462-009 | Form: LOTION
Manufacturer: SORA KOZMETIK SANAYI TICARET ANONIM SIRKETI
Category: otc | Type: HUMAN OTC DRUG LABEL
Date: 20200716

ACTIVE INGREDIENTS: OXYBENZONE 17 g/200 g
INACTIVE INGREDIENTS: FRUCTOSE; TROLAMINE; AVOBENZONE; XANTHAN GUM; SODIUM ACETATE; CARROT; ALPHA-TOCOPHEROL ACETATE; WATER; GLYCERYL STEARATE SE; HOMOSALATE; SUNFLOWER OIL; POWDERED CELLULOSE; .BETA.-CAROTENE; OCTOCRYLENE; PEG-100 STEARATE; POLYOXYL 20 CETOSTEARYL ETHER; ETHYLHEXYL PALMITATE; HYDROXYETHYL CELLULOSE, UNSPECIFIED; CETOSTEARYL ALCOHOL; CHLORPHENESIN; ENSULIZOLE; PHENOXYETHANOL; INULIN; GLYCERIN; ALKYL (C12-15) BENZOATE; CYCLOMETHICONE 5; TRIMETHYLSILOXYSILICATE (M/Q 0.6-0.8)

Bebak Baby Sun

Active Ingredient

Oxybenzone.......8.5%

Purpose

Sunscreen

Uses

Provides a high degree of protection against the harmful UVA and UVB rays of the sun

Warnings

For external use only
In case of an undesired effect regarding the use of the product, consult a doctor. Avoid long-term sunbathing and midday sun even if you had put on sunscreen. Use the product with the sun protections factor suitable for your skin.

WHEN USING

Avoid eye contact and do not spray directly on the face, in case of eye contact rinse with plenty of water.

Keep out of reach of children.

Directions

Apply a sufficient quantity of the product evenly on clean and dry skin before going out in the sun. Repeat application frequently.

Inactive Ingredients

Aqua, Benzophenone-3, Octocrylene, Glyceryl Stearate, Homosalate, Butyl Methoxydibenzoylmethane, PEG-100 Stearate, Cetearyl Alcohol, Ceteareth-20, C12-15 Alkyl Benzoate, Cyclopentasiloxane, Ethylhexyl Palmitate, Trimethylsiloxysilicate, Phenylbenzimidazole Sulfonic Acid, Phenoxyethanol, Triethanolamine, Inulin, Chlorphenesin, Xanthan Gum, Glycerin, Fructose, Hydroxyethylcellulose, Helianthus Annuus Seed Oil, Sodium Acetate, Cellulose, Daucus Carota Sativa Extract, Beta-Carotene, Tocopheryl Acetate